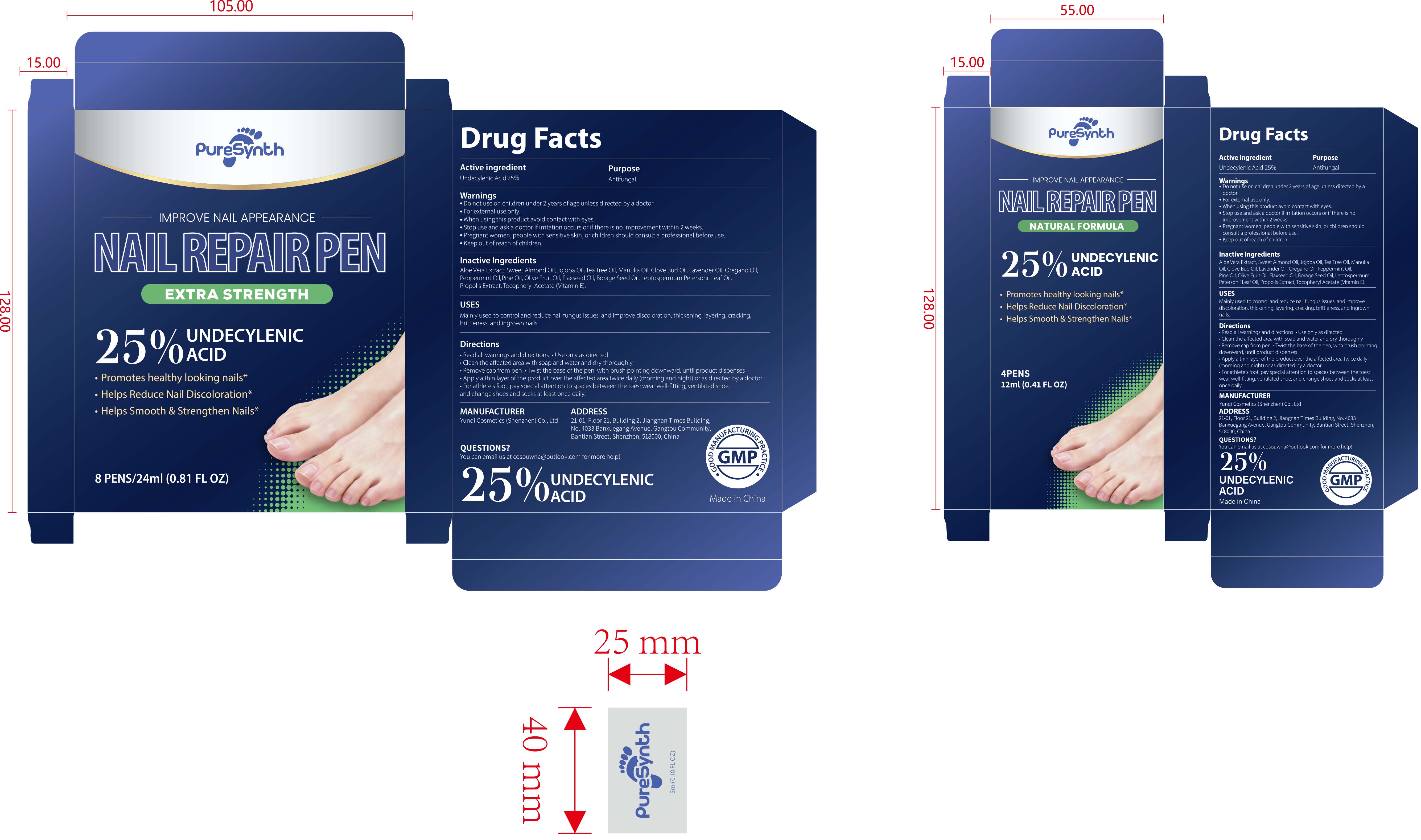 DRUG LABEL: NAIL REPAIR PEN
NDC: 84763-008 | Form: LIQUID
Manufacturer: Yunqi Cosmetics (Shenzhen) Co., Ltd
Category: otc | Type: HUMAN OTC DRUG LABEL
Date: 20251209

ACTIVE INGREDIENTS: UNDECYLENIC ACID 0.25 g/1 mL
INACTIVE INGREDIENTS: LAVENDER OIL; ALOE VERA LEAF; OLIVE OIL; WHITE PINE OIL; .ALPHA.-TOCOPHEROL ACETATE; PROPOLIS WAX; BORAGE SEED OIL; JOJOBA OIL; LEPTOSPERMUM PETERSONII LEAF OIL; ALMOND OIL; MANUKA OIL; CLOVE OIL; OREGANO LEAF OIL; PEPPERMINT OIL; LINSEED OIL; TEA TREE OIL

84763-008 NAIL REPAIR PEN

ACTIVE INGREDIENT

Undecylenic Acid 25%

PURPOSE

Antifungal

INDICATIONS AND USAGE

Mainly used to control and reduce nail fungus issues, and improve discoloration, thickening, layering, cracking
brittleness, and ingrown nails.

WARNINGS

For external use only.

Do not use on children under 2 years of age unless directed by a doctor.

When using this product avoid contact with eyes.
Pregnant women, people with sensitive skin, or children should consult a professional before use.

Stop use and ask a doctor lf irritation occurs or if there is no improvement within 2 weeks.

Keep out of reach of children.

DOSAGE AND ADMINISTRATION

Read all warnings and directions ·Use only as directed
Clean the affected area with soap and water and dry thoroughly
Remove cap from pen .Twist the base of the pen, with brush pointing downward, until product dispenses
Apply a thin laver of the product over the affected area twice daily (morning and night) or as directed by a doctor
For athlete's foot, pay special attention to spaces between the toes; wear well-ftting, ventilated shoe. and change shoes and socks at least once daily.

INACTIVE INGREDIENT

Aloe Vera Extract
Sweet Almond Oil
Jojoba Oil
Tea Tree Oil
Manuka Oil
Clove Bud Oil
Lavender Oil
Oregano Oil
Peppermint Oil
Pine Oil
Olive Fruit Oil
Flaxseed Oil
Borage Seed Oil
Leptospermum Petersonii Leaf Oil
Propolis Extract
Tocopheryl Acetate (Vitamin E)